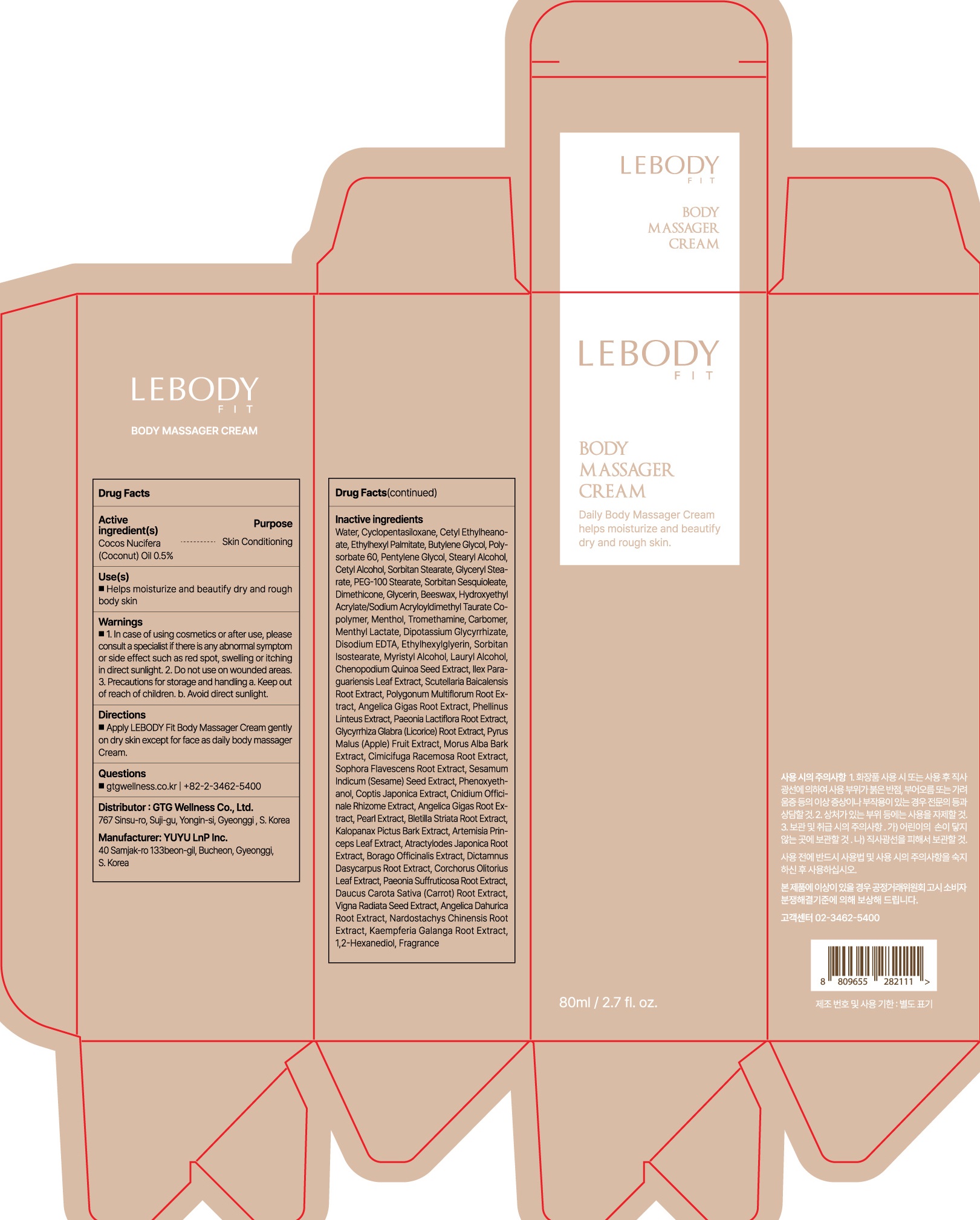 DRUG LABEL: LEBODY FIT BODY MASSAGER
NDC: 71080-0030 | Form: CREAM
Manufacturer: GTG WELLNESS CO., LTD.
Category: otc | Type: HUMAN OTC DRUG LABEL
Date: 20230315

ACTIVE INGREDIENTS: COCONUT OIL 0.5 g/100 mL
INACTIVE INGREDIENTS: Water; CYCLOMETHICONE 5; Cetyl Ethylhexanoate; Ethylhexyl Palmitate

ACTIVE INGREDIENT

Cocos Nucifera (Coconut) Oil 0.5%

INACTIVE INGREDIENTS

Water, Cyclopentasiloxane, Cetyl Ethylhexanoate, Ethylhexyl Palmitate, Butylene Glycol, Polysorbate 60, Pentylene Glycol, Stearyl Alcohol, Cetyl Alcohol, Sorbitan Stearate, Glyceryl Stearate, PEG-100 Stearate, Sorbitan Sesquioleate, Dimethicone, Glycerin, Beeswax, Hydroxyethyl Acrylate/Sodium Acryloyldimethyl Taurate Copolymer, Menthol, Tromethamine, Carbomer, Menthyl Lactate, Dipotassium Glycyrrhizate, Disodium EDTA, Ethylhexylglycerin, Sorbitan Isostearate, Myristyl Alcohol, Lauryl Alcohol, Chenopodium Quinoa Seed Extract, Ilex Paraguariensis Leaf Extract, Scutellaria Baicalensis Root Extract, Polygonum Multiflorum Root Extract, Angelica Gigas Root Extract, Phellinus Linteus Extract, Paeonia Lactiflora Root Extract, Glycyrrhiza Glabra (Licorice) Root Extract, Pyrus Malus (Apple) Fruit Extract, Morus Alba Bark Extract, Cimicifuga Racemosa Root Extract, Sophora Flavescens Root Extract, Sesamum Indicum (Sesame) Seed Extract, Phenoxyethanol, Coptis Japonica Extract, Cnidium Officinale Rhizome Extract, Angelica Gigas Root Extract, Pearl Extract, Bletilla Striata Root Extract, Kalopanax Pictus Bark Extract, Artemisia Princeps Leaf Extract, Atractylodes Japonica Root Extract, Borago Officinalis Extract, Dictamnus Dasycarpus Root Extract, Corchorus Olitorius Leaf Extract, Paeonia Suffruticosa Root Extract, Daucus Carota Sativa (Carrot) Root Extract, Vigna Radiata Seed Extract, Angelica Dahurica Root Extract, Nardostachys Chinensis Root Extract, Kaempferia Galanga Root Extract, 1,2-Hexanediol, Fragrance

PURPOSE

Skin Conditioning

WARNINGS

1. In case of using cosmetics or after use, please consult a specialist if there is any abnormal symptom or side effect such as red spot, swelling or itching in direct sunlight. 2. Do not use on wounded areas.
3. Precautions for storage and handling a. Keep out of reach of children. b. Avoid direct sunlight.

KEEP OUT OF REACH OF CHILDREN

Uses

■ Helps moisturize and beautify dry and rough body skin

Directions

■ Apply LEBODY Fit Body Massager Cream gently on dry skin except for face as daily body massager cream.

Questions

■ gtgwellness.co.kr | +82-2-3462-5400